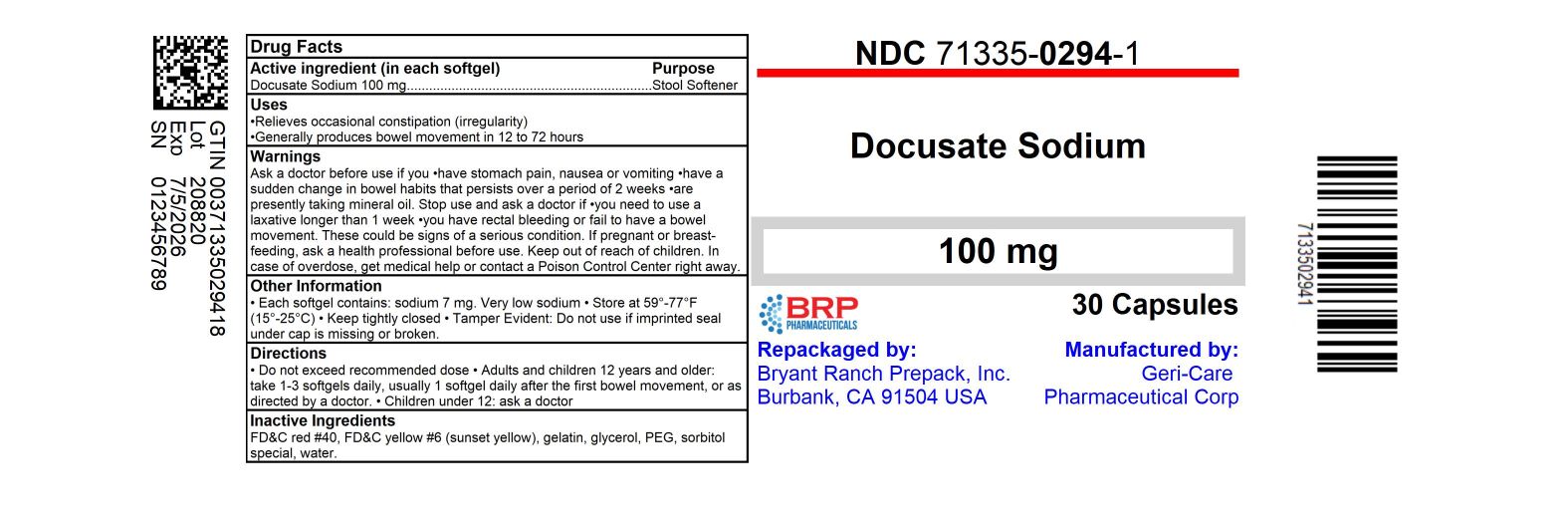 DRUG LABEL: Stool Softener
NDC: 71335-0294 | Form: CAPSULE, LIQUID FILLED
Manufacturer: Bryant Ranch Prepack
Category: otc | Type: HUMAN OTC DRUG LABEL
Date: 20240705

ACTIVE INGREDIENTS: DOCUSATE SODIUM 100 mg/1 1
INACTIVE INGREDIENTS: FD&C RED NO. 40; GELATIN, UNSPECIFIED; GLYCERIN; POLYETHYLENE GLYCOL 400; SORBITOL; WATER; FD&C YELLOW NO. 6; MANNITOL

gc 401

Active ingredient (in each softgel)

Docusate Sodium 100 mg

Purpose

Stool Softener Laxative

Uses

- relieves occasional constipation (irregularity)

- generally produces bowel movement in 12 to 72 hours

Warnings

Ask a doctor before use if you

• have stomach pain, nausea or vomiting

• have a sudden change in bowel habits that persists over a period of 2 weeks

• are presently taking mineral oil

Stop use and ask a doctor if

• you need to use a laxative longer than 1 week

• you have rectal bleeding or fail to have a bowel movement. These

could be signs of a serious condition.

If pregnant or breast-feeding, ask a health professional before use.

Keep out of reach of children. In case of overdose, get medical help or contact a Poison Control Center right away.

Directions

• do not exceed recommended dose
• adults and children 12 years and older: take 1-3
softgels daily until first bowel movement; 1 softgel
daily thereafter, or as directed by a doctor
• children under 12: consult a doctor

Other information

• each softgel contains: sodium 7 mg. Very low sodium
• store at 59°-77°F (15°-25°C)
• keep tightly closed
• Tamper Evident: Do not use if imprinted seal
under cap is missing or broken.

Inactive ingredients

FD&C red #40, FD&C yellow #6 (sunset yellow), gelatin, glycerin, PEG, sorbitol special, water.

HOW SUPPLIED

Docusate Sodium 100mg Capsule

- NDC: 71335-0294-1: 30 Tablets in a BOTTLE
- NDC: 71335-0294-2: 100 Tablets in a BOTTLE
- NDC: 71335-0294-3: 60 Tablets in a BOTTLE
- NDC: 71335-0294-4: 120 Tablets in a BOTTLE
- NDC: 71335-0294-5: 90 Tablets in a BOTTLE
- NDC: 71335-0294-6: 180 Tablets in a BOTTLE
- NDC: 71335-0294-7: 10 Tablets in a BOTTLE
- NDC: 71335-0294-8: 28 Tablets in a BOTTLE
- NDC: 71335-0294-9: 56 Tablets in a BOTTLE
- NDC: 71335-0294-0: 18 Tablets in a BOTTLE

Repackaged/Relabeled by:
Bryant Ranch Prepack, Inc.
Burbank, CA 91504

PACKAGE LABEL

Docusate Sodium 100mg Capsule